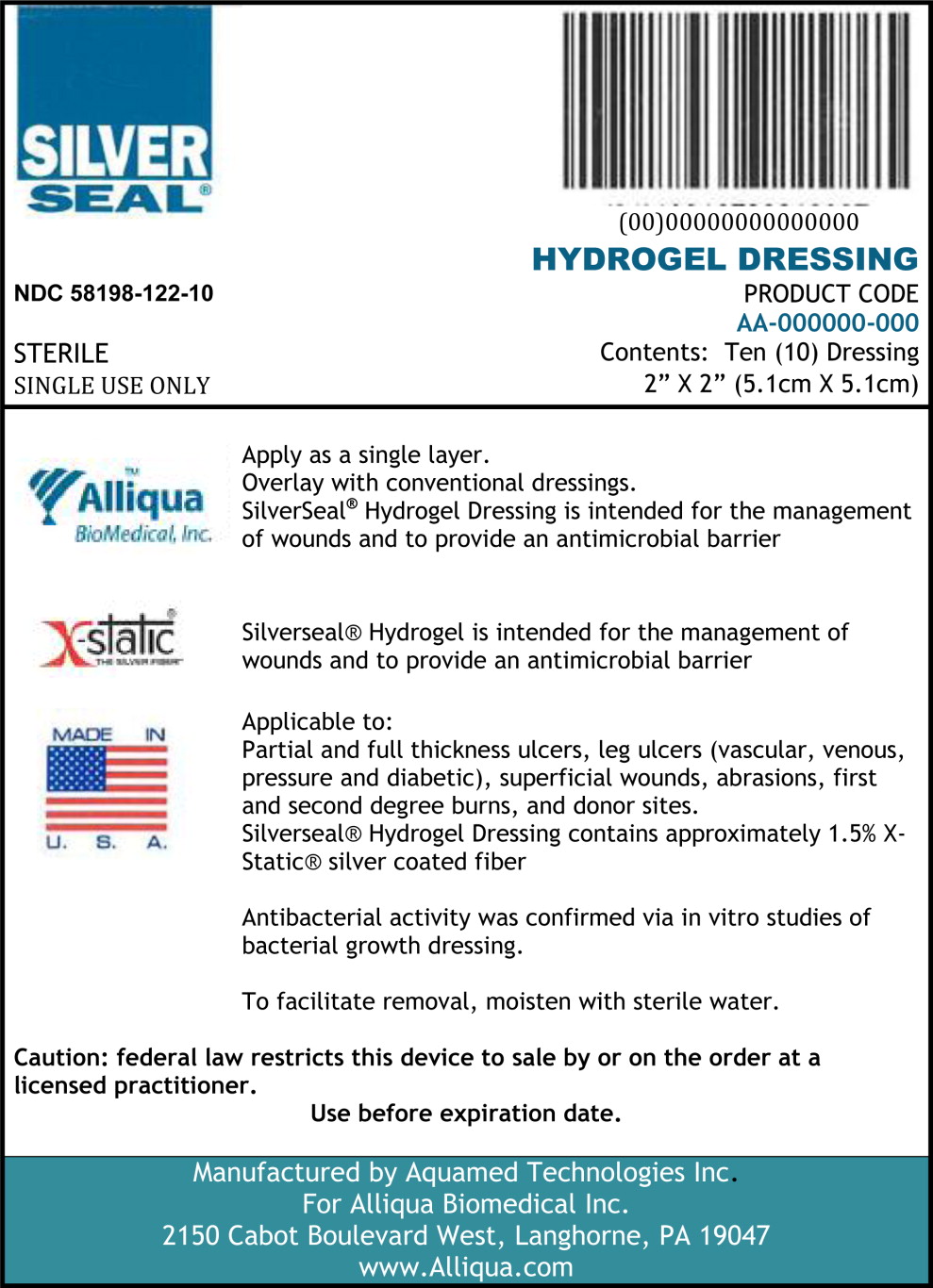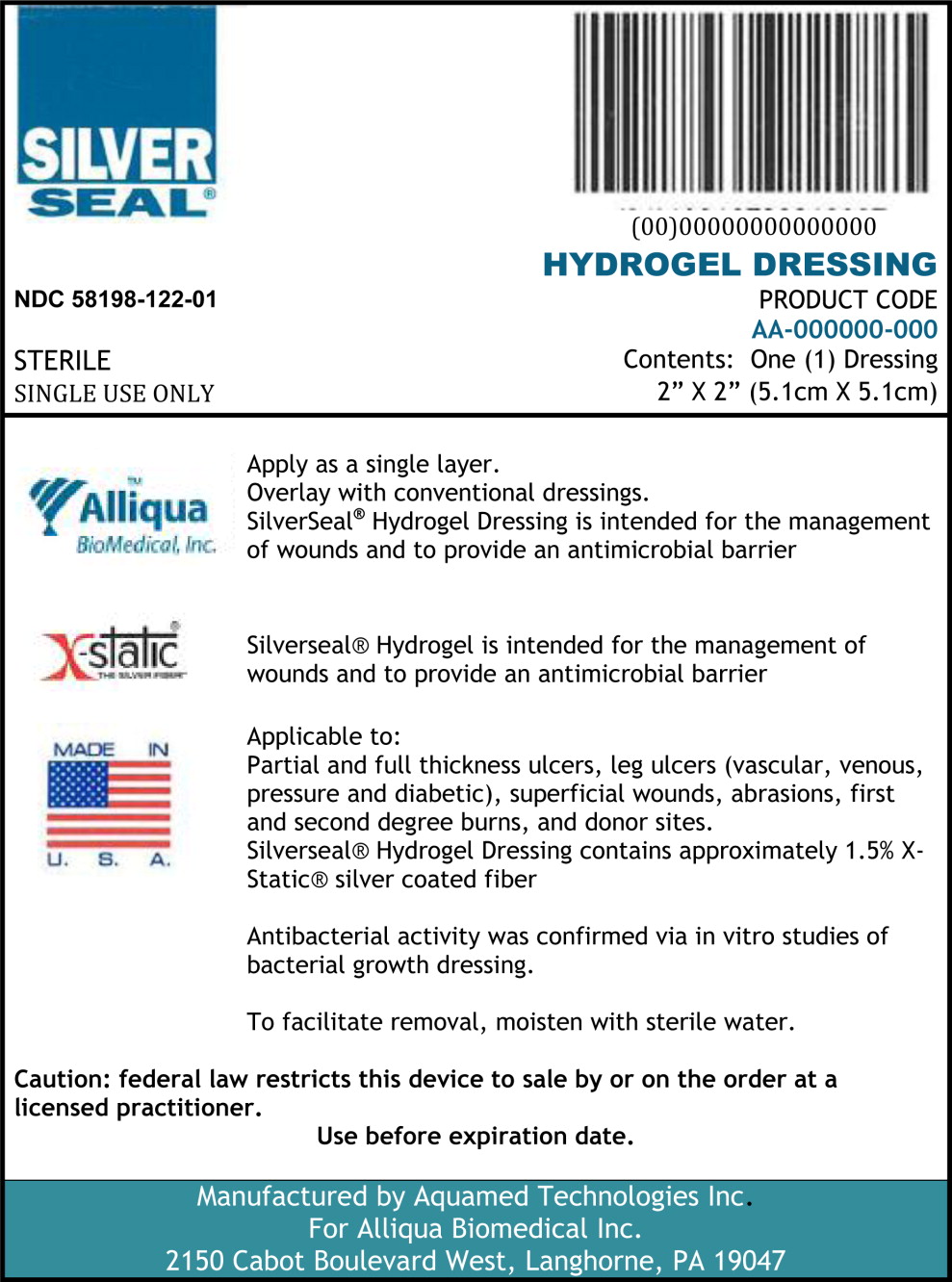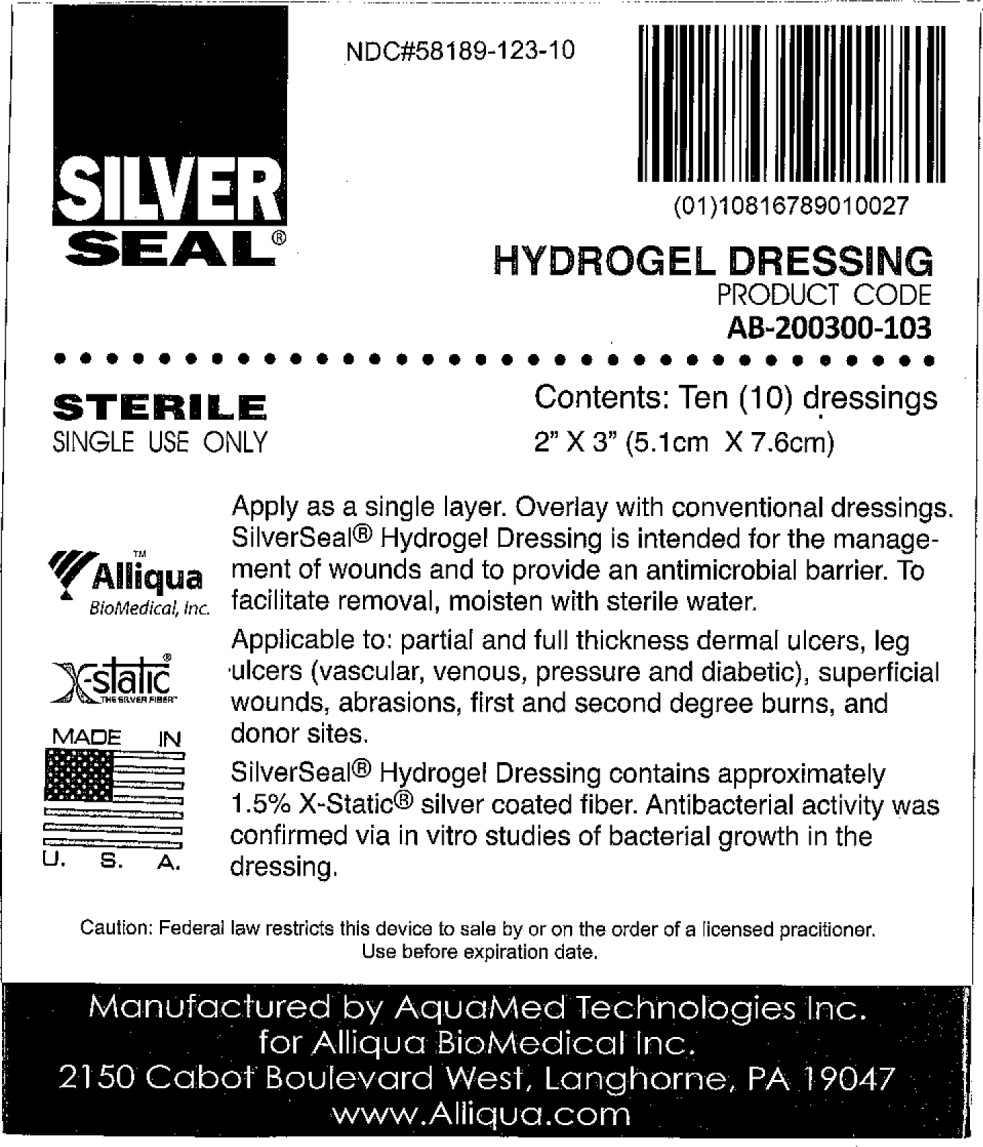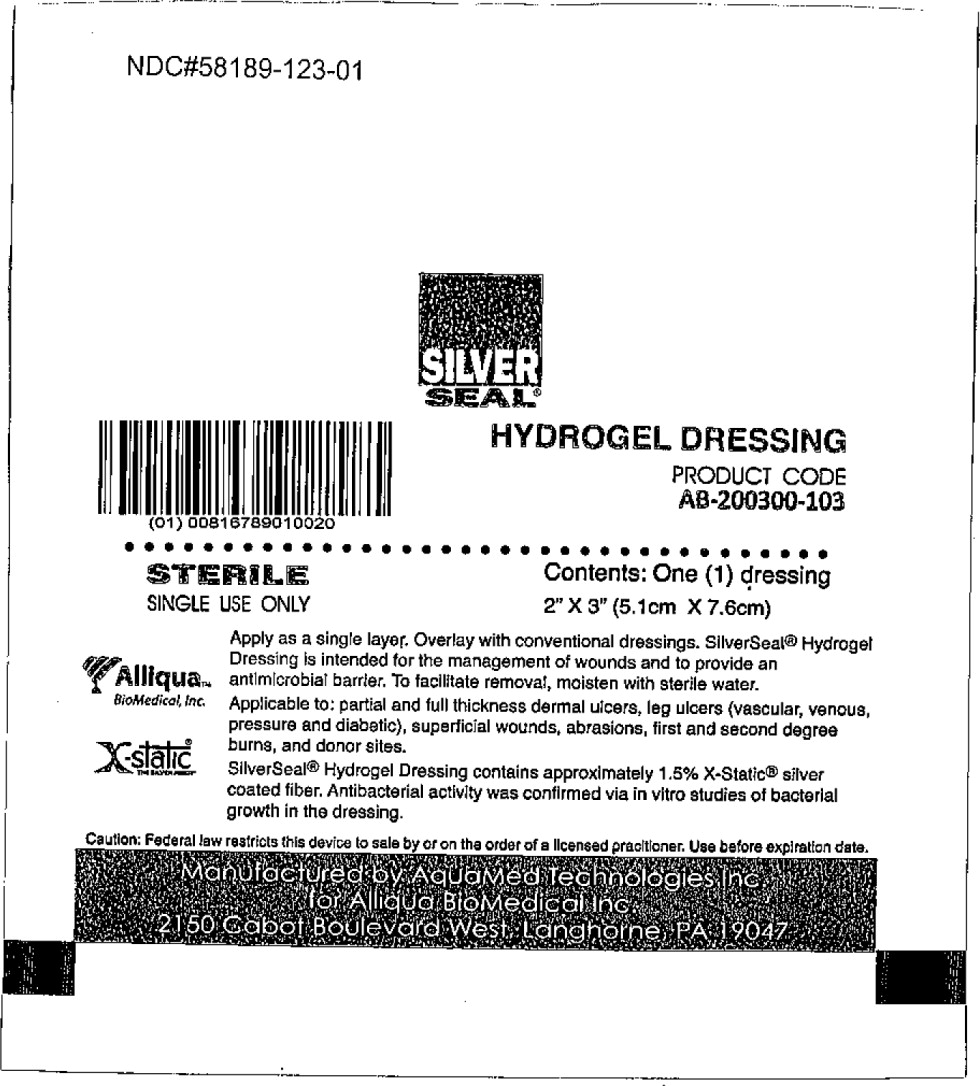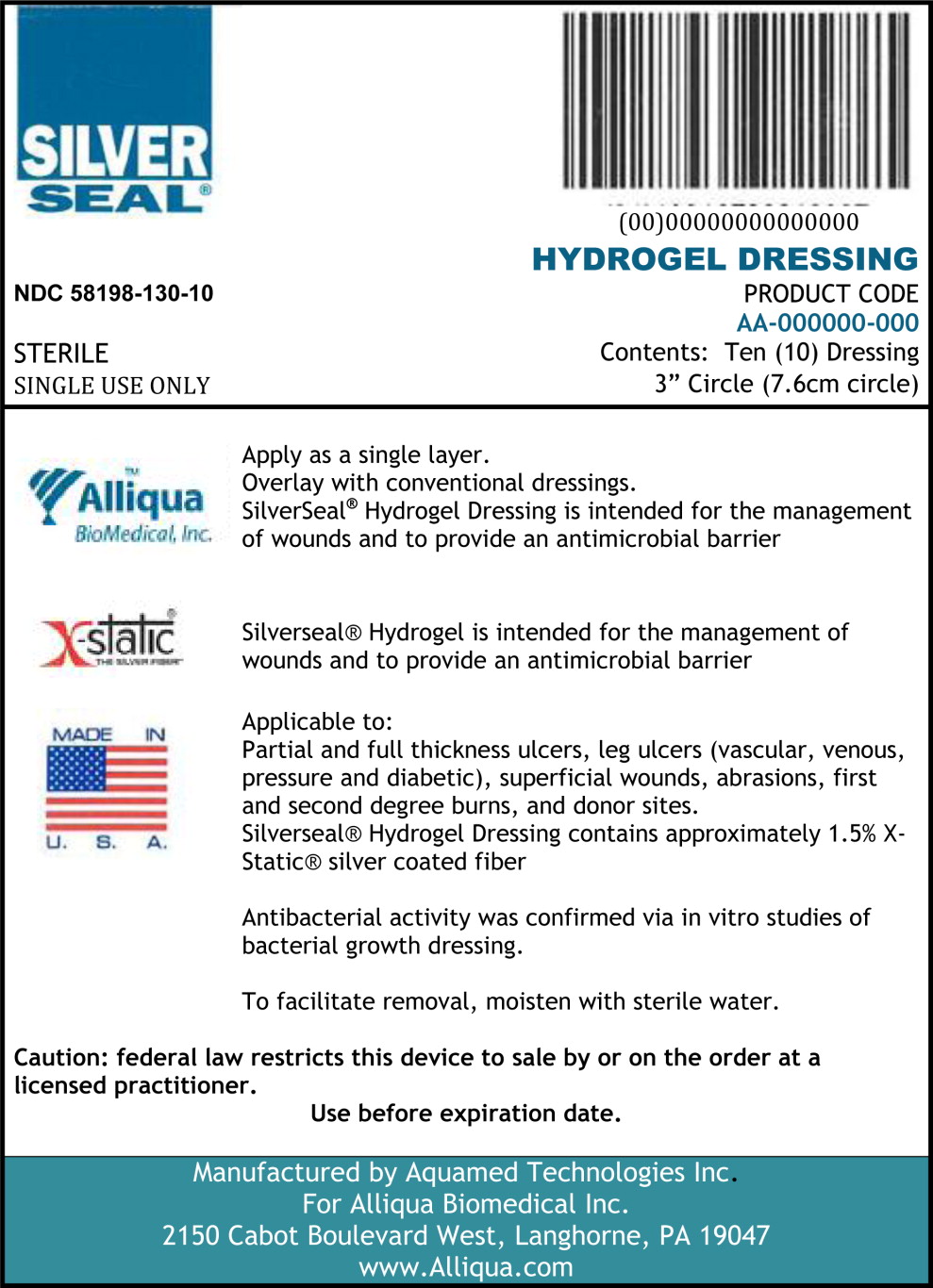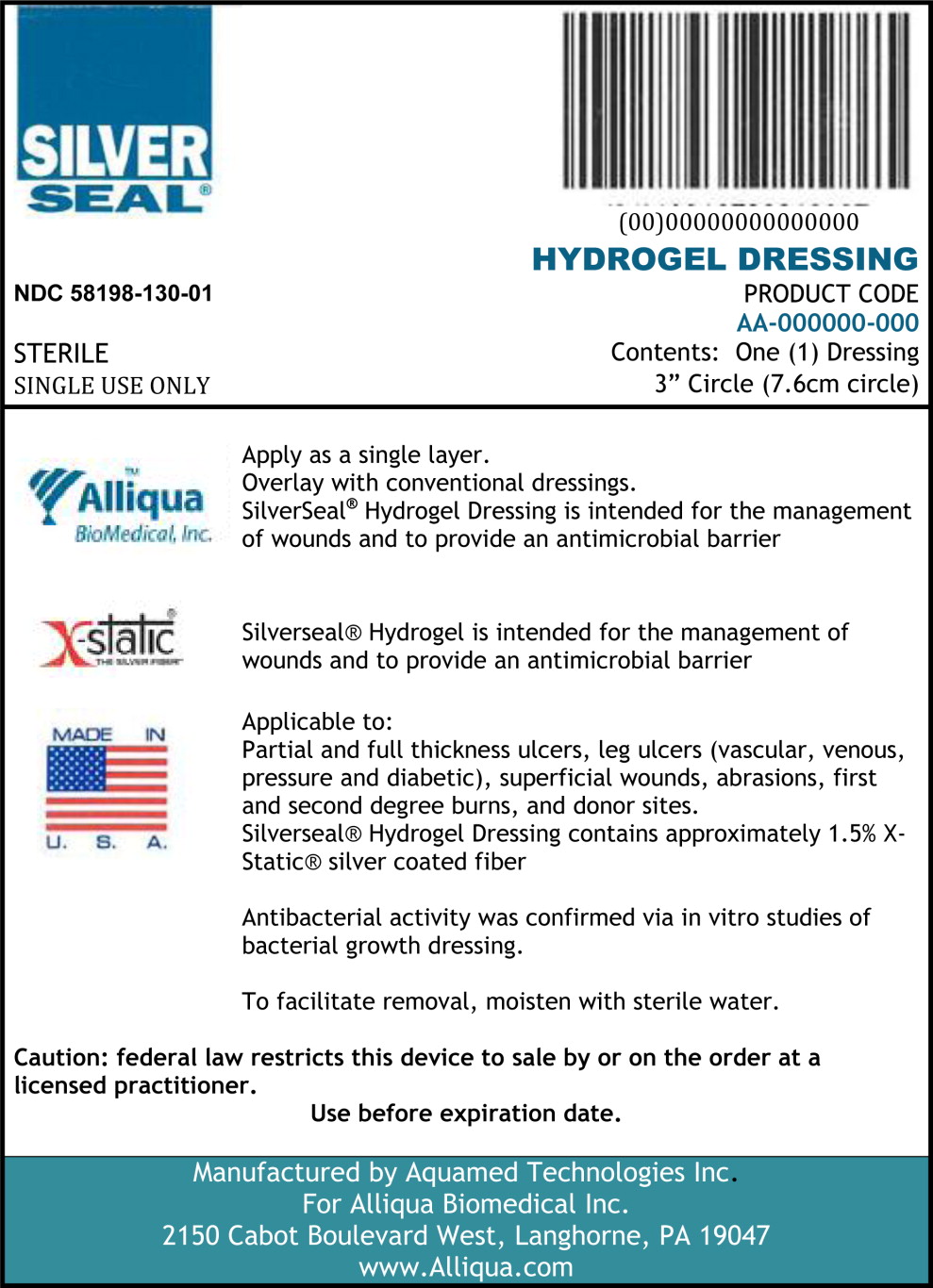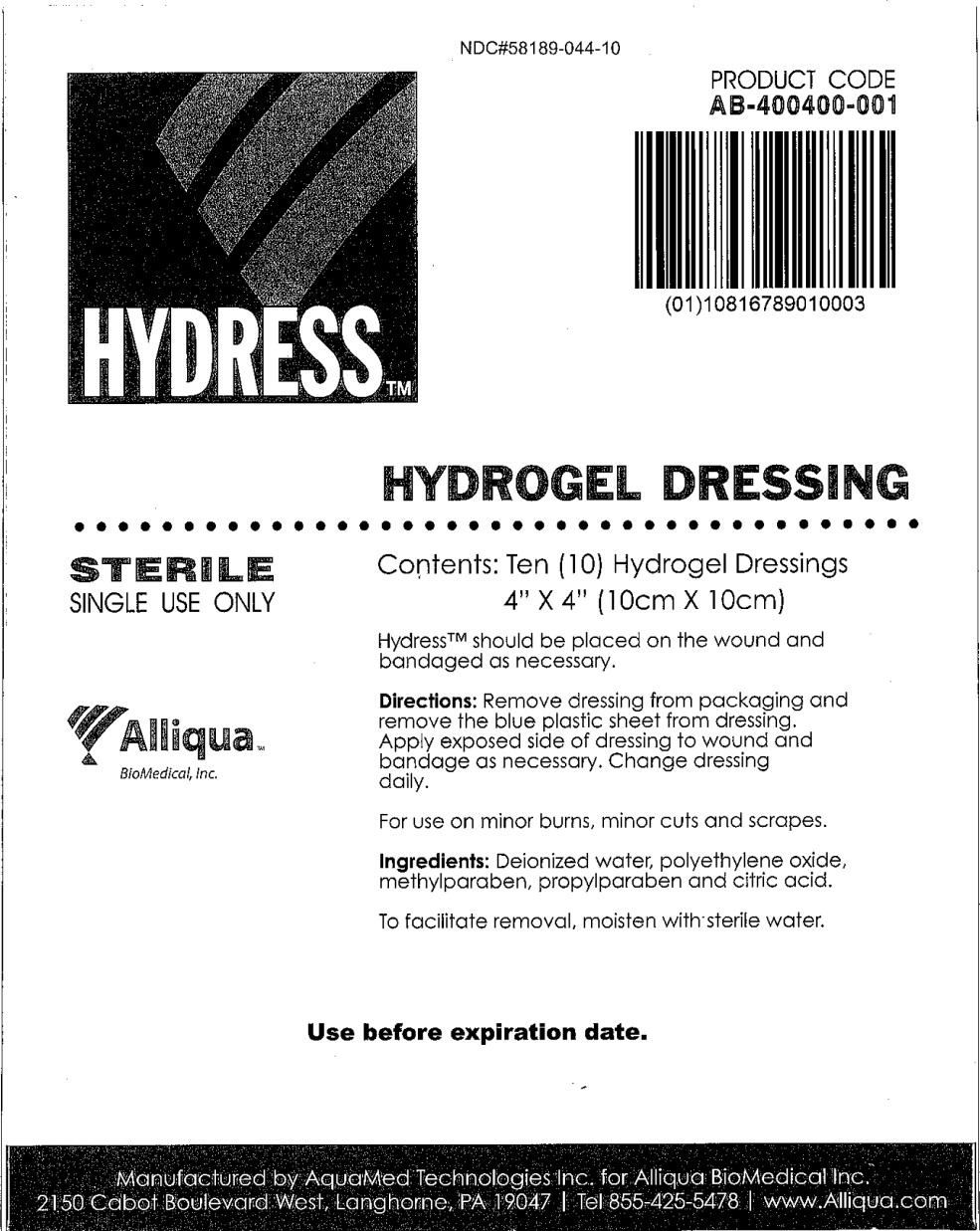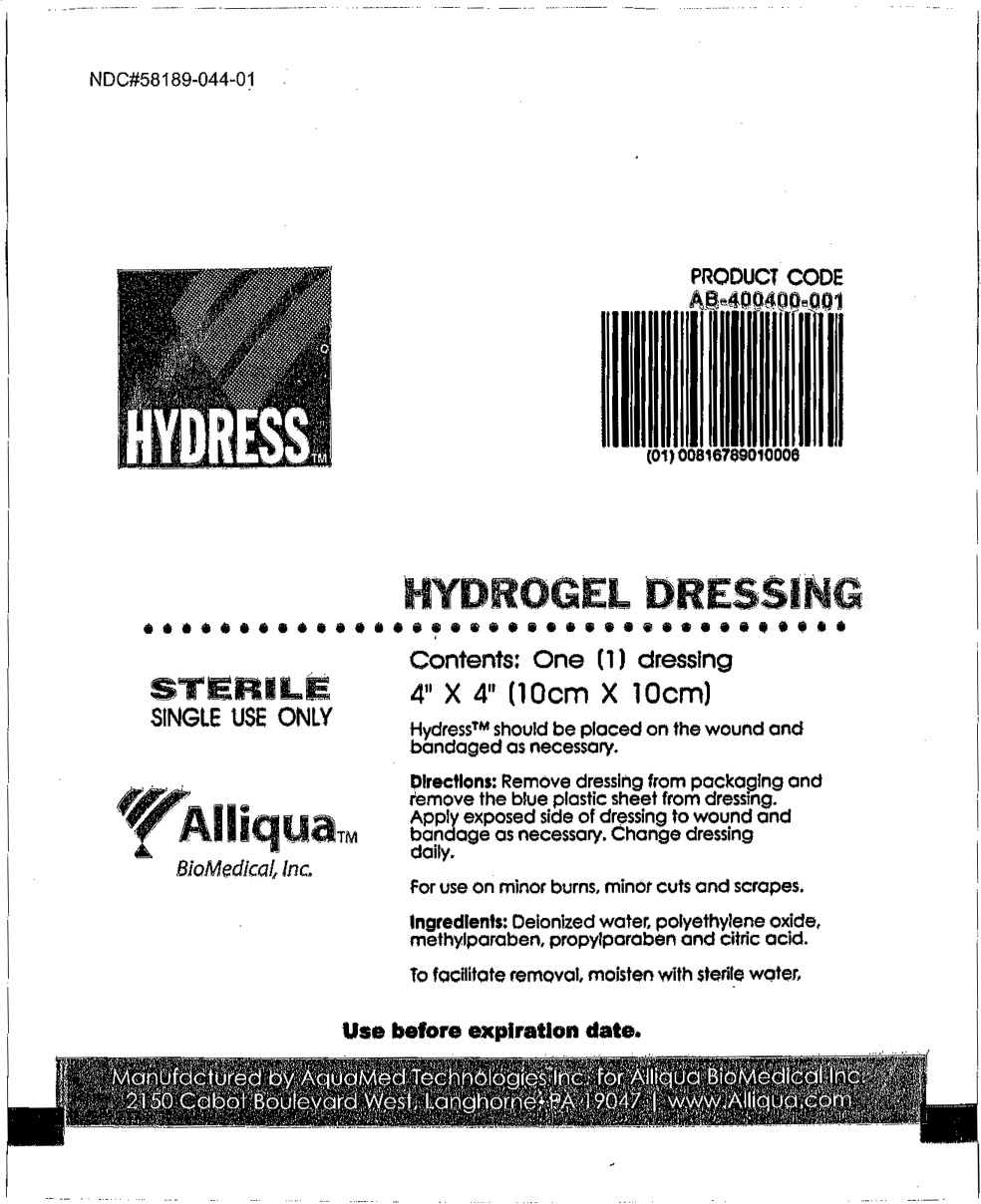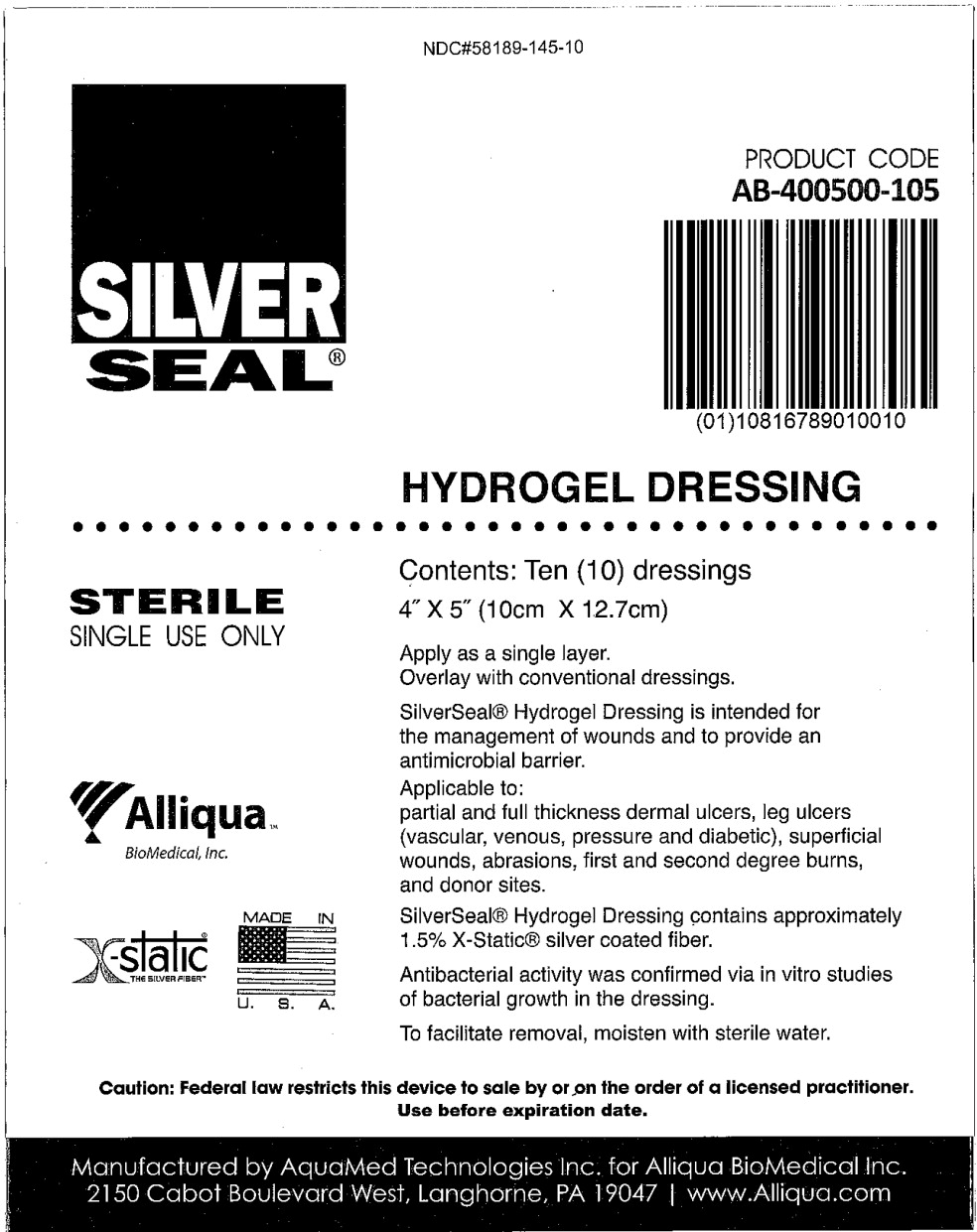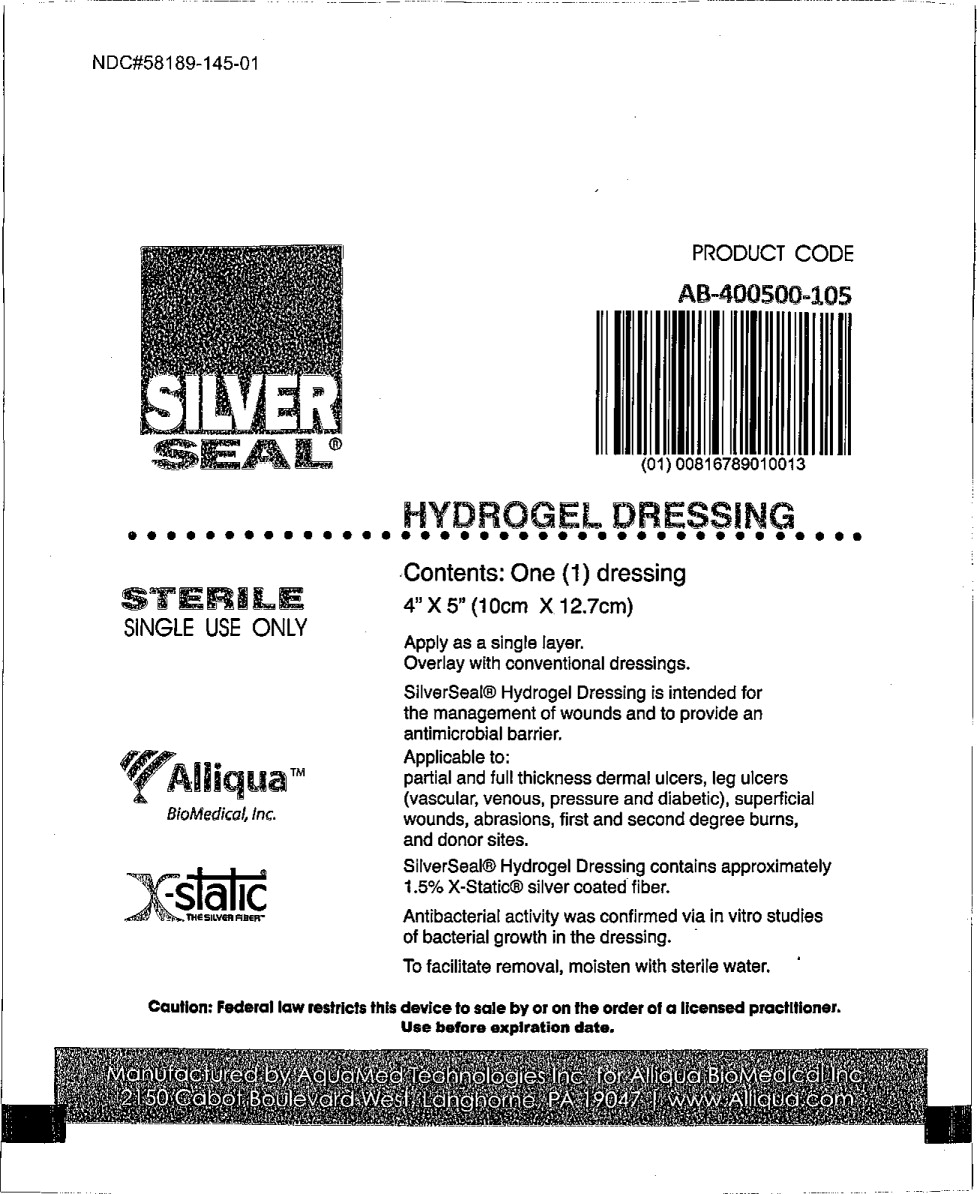 DRUG LABEL: X-static Silverseal hydrogel dressing 4 X 5
NDC: 58189-145
Manufacturer: Alliqua Inc
Category: other | Type: MEDICAL DEVICE
Date: 20130507

HYDROGEL DRESSING

Apply as a single layer.

Overlay with conventional dressings.

SilverSeal® Hydrogel Dressing is intended for the management of wounds and to provide an antimicrobial barrier

Silverseal® Hydrogel is intended for the management of wounds and to provide an antimicrobial barrier

Applicable to:

Partial and full thickness ulcers, leg ulcers (vascular, venous, pressure and diabetic), superficial wounds, abrasions, first and second degree burns, and donor sites.
Silverseal® Hydrogel Dressing contains approximately 1.5% X-Static® silver coated fiber

Antibacterial activity was confirmed via in vitro studies of bacterial growth dressing.

To facilitate removal, moisten with sterile water.

Caution: federal law restricts this device to sale by or on the order at a licensed practitioner.

Use before expiration date.

Principal Display Panel – 2” X 2” Dressing Box Label

SILVER
SEAL®

(00)00000000000000
HYDROGEL DRESSING
NDC 58198-122-10 PRODUCT CODE
AA-000000-000
STERILE Contents: Ten (10) Dressing
SINGLE USE ONLY 2” X 2” (5.1cm X 5.1cm)

Manufactured by Aquamed Technologies Inc.
For Alliqua Biomedical Inc.
2150 Cabot Boulevard West, Langhorne, PA 19047
www.Alliqua.com

Principal Display Panel – 2” X 2” Dressing Pouch Label

SILVER
SEAL®

(00)00000000000000
HYDROGEL DRESSING
NDC 58198-122-01 PRODUCT CODE
AA-000000-000
STERILE Contents: One (1) Dressing
SINGLE USE ONLY 2” X 2” (5.1cm X 5.1cm)

Manufactured by Aquamed Technologies Inc.
For Alliqua Biomedical Inc.
2150 Cabot Boulevard West, Langhorne, PA 19047
www.Alliqua.com

Principal Display Panel – 2” X 3” Dressing Box Label

NDC 58198-123-10

SILVER
SEAL®

(01)10816789010027

HYDROGEL DRESSING

PRODUCT CODE
AB-200300-103

STERILE Contents: Ten (10) dressings
SINGLE USE ONLY 2” X 3” (5.1cm X 7.6cm)

Manufactured by Aquamed Technologies Inc.

for Alliqua Biomedical Inc.
2150 Cabot Boulevard West, Langhorne, PA 19047

www.Alliqua.com

Principal Display Panel – 4” X 5” Dressing Box Label

NDC 58198-123-01

SILVER
SEAL®

(01)00816789010020 HYDROGEL DRESSING

PRODUCT CODE
AB-200300-103

STERILE Contents: One (1) dressing
SINGLE USE ONLY 2” X 3” (5.1cm X 7.6cm)

Manufactured by Aquamed Technologies Inc.

for Alliqua Biomedical Inc.
2150 Cabot Boulevard West, Langhorne, PA 19047

Principal Display Panel – 3” Circle Dressing Box Label

SILVER
SEAL®

(00)00000000000000
HYDROGEL DRESSING
NDC 58198-130-10 PRODUCT CODE
AA-000000-000
STERILE Contents: Ten (10) Dressing
SINGLE USE ONLY 3” Circle (7.6cm circle)

Manufactured by Aquamed Technologies Inc.
For Alliqua Biomedical Inc.
2150 Cabot Boulevard West, Langhorne, PA 19047
www.Alliqua.com

Principal Display Panel – 3” Circle Dressing Pouch Label

SILVER
SEAL®

(00)00000000000000
HYDROGEL DRESSING
NDC 58198-130-01 PRODUCT CODE
AA-000000-000
STERILE Contents: One (1) Dressing
SINGLE USE ONLY 3” Circle (7.6cm circle)

Manufactured by Aquamed Technologies Inc.
For Alliqua Biomedical Inc.
2150 Cabot Boulevard West, Langhorne, PA 19047
www.Alliqua.com

Principal Display Panel – 4” X 4" Circle Dressing Box Label

NDC 58198-044-10 PRODUCT CODE

AB-400400-001

HYDRESSTM

(01)10816789010003
HYDROGEL DRESSING
STERILE Contents: Ten (10) Hydrogel Dressings
SINGLE USE ONLY 4” X 4” (10cm X 10cm)

Manufactured by Aquamed Technologies Inc. for Alliqua Biomedical Inc.
2150 Cabot Boulevard West, Langhorne, PA 19047 | Tel 855-425-5478 | www.Alliqua.com

Principal Display Panel – 4” X 4" Circle Dressing Pouch Label

NDC 58198-044-10 PRODUCT CODE

AB-400400-001

HYDRESSTM

(01)00816789010006
HYDROGEL DRESSING
STERILE Contents: One (1) dressing
SINGLE USE ONLY 4” X 4” (10cm X 10cm)

Manufactured by Aquamed Technologies Inc. for Alliqua Biomedical Inc.
2150 Cabot Boulevard West, Langhorne, PA 19047 | Tel 855-425-5478 | www.Alliqua.com

Principal Display Panel – 4” X 5” Dressing Box Label

NDC 58198-145-10

SILVER
SEAL®

PRODUCT CODE
AB-400500-105

(01)10816789010010

HYDROGEL DRESSING
STERILE Contents: Ten (10) dressings
SINGLE USE ONLY 4” X 5” (10cm X 12.7cm)

Manufactured by Aquamed Technologies Inc. for Alliqua Biomedical Inc.
2150 Cabot Boulevard West, Langhorne, PA 19047 | www.Alliqua.com

Principal Display Panel – 4” X 5” Dressing Box Label

NDC 58198-145-01

SILVER
SEAL®

PRODUCT CODE
AB-400500-105

(01)00816789010013

HYDROGEL DRESSING
STERILE Contents: One (1) dressing
SINGLE USE ONLY 4” X 5” (10cm X 12.7cm)

Manufactured by Aquamed Technologies Inc. for Alliqua Biomedical Inc.
2150 Cabot Boulevard West, Langhorne, PA 19047 | www.Alliqua.com